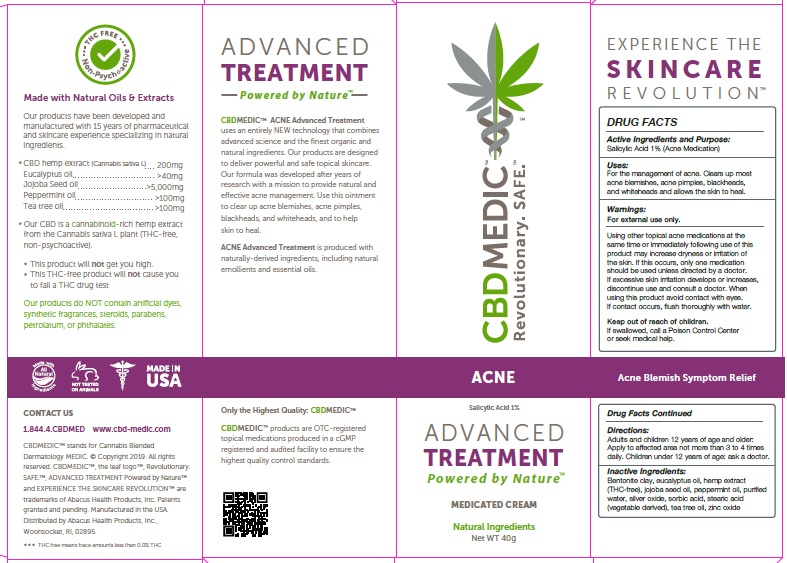 DRUG LABEL: CBDMEDIC Acne Treatment
NDC: 24909-732 | Form: OINTMENT
Manufacturer: AIDANCE SKINCARE & TOPICAL SOLUTIONS, LLC
Category: otc | Type: HUMAN OTC DRUG LABEL
Date: 20190306

ACTIVE INGREDIENTS: SALICYLIC ACID 10 mg/1 g
INACTIVE INGREDIENTS: BENTONITE; EUCALYPTUS OIL; HEMP; JOJOBA OIL; PEPPERMINT OIL; WATER; SILVER OXIDE; SORBIC ACID; STEARIC ACID; TEA TREE OIL; ZINC OXIDE

CBDMEDIC Acne Treatment

Active Ingredients and Purpose

Salicylic Acid 1% (Acne Medication)

Uses

For the management of acne. Clears up most acne blemishes, acne pimples, blackheads, and whiteheads and allows the skin to heal.

Warnings

For external use only. Using other topical acne medications at the same time or immediately following use of this product may increase dryness or irritation of the skin. If this occurs, only one medication should be used unless directed by a doctor. If excessive skin irritation develops or increases, discontinue use and consult a doctor. When using this product avoid contact with eyes. If contact occurs, flush thoroughly with water.

Keep out of reach of children. If swallowed, call a Poison Control Center or seek medical help.

Directions:

Adults and children 12 years of age and older: Apply to affected area not more than 3 to 4 times daily. Children under 12 years of age: ask a doctor.

Inactive ingredients

Bentonite clay, eucalyptus oil, hemp extract (THC-free), jojoba seed oil, peppermint oil, purified water, silver oxide, sorbic acid, stearic acid
(vegetable derived), tea tree oil, zinc oxide